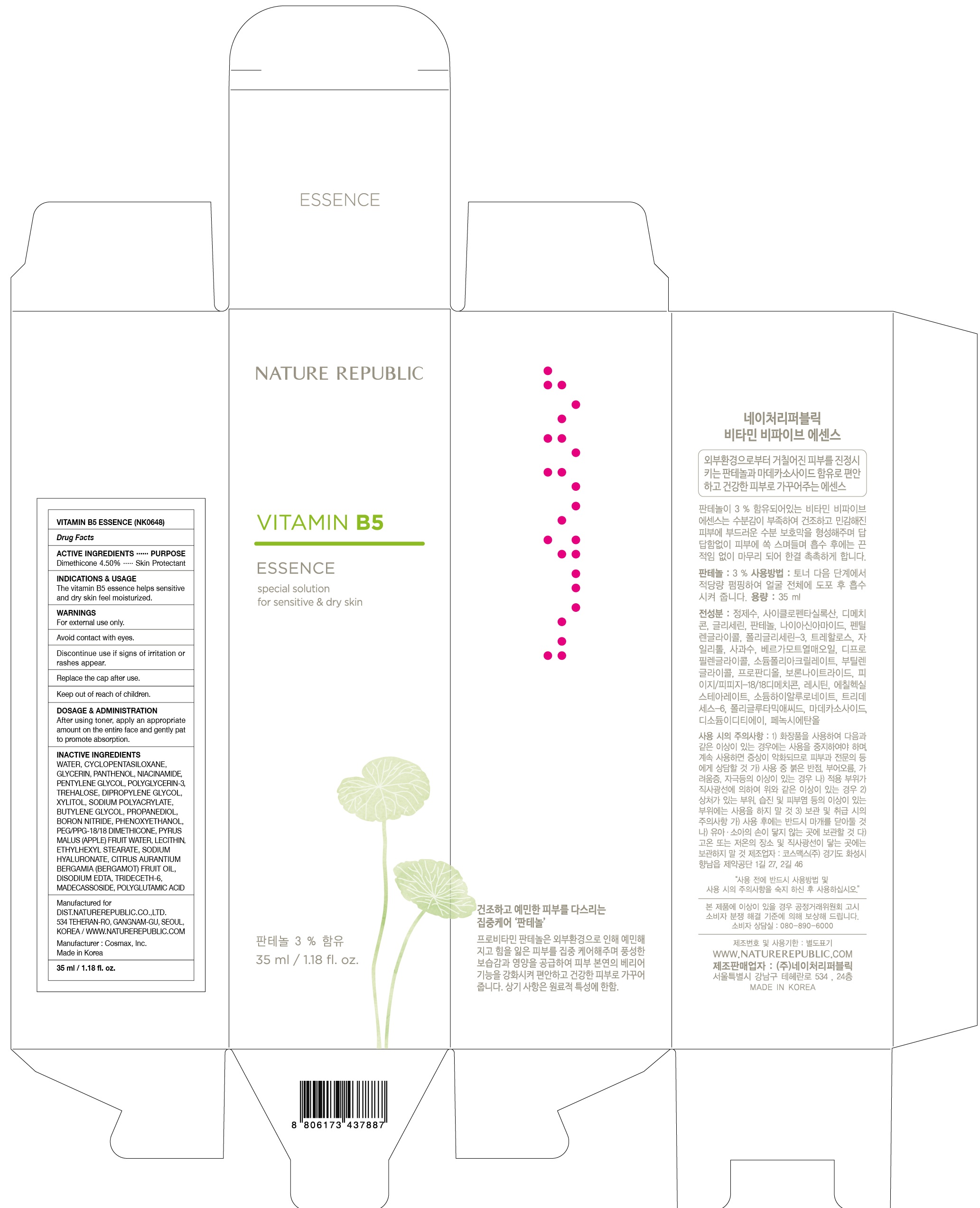 DRUG LABEL: VITAMIN B5 ESSENCE
NDC: 51346-436 | Form: CREAM
Manufacturer: NATURE REPUBLIC CO., LTD.
Category: otc | Type: HUMAN OTC DRUG LABEL
Date: 20170119

ACTIVE INGREDIENTS: Dimethicone 1.57 g/35 mL
INACTIVE INGREDIENTS: Water; Glycerin

ACTIVE INGREDIENT

Active ingredients: Dimethicone 4.50%

INACTIVE INGREDIENT

Inactive ingredients: Water, Cyclopentasiloxane, Glycerin, Panthenol, Niacinamide, Pentylene Glycol, Polyglycerin-3, Trehalose, Dipropylene Glycol, Xylitol, Sodium Polyacrylate, Butylene Glycol, Propanediol, Boron Nitride, Phenoxyethanol, PEG/PPG-18/18 Dimethicone, Pyrus Malus (Apple) Fruit Water, Lecithin, Ethylhexyl Stearate, Sodium Hyaluronate, Citrus Aurantium Bergamia (Bergamot) Fruit Oil, Disodium EDTA, Trideceth-6, Madecassoside, Polyglutamic Acid

PURPOSE

Purpose: Skin Protectant

WARNINGS

Warnings: For external use only. Avoid contact with eyes and mouth. Discontinue use if signs of irritation or rashes appear. Keep out of reach of children. Replace the cap after use.

KEEP OUT OF REACH OF CHILDREN

INDICATIONS & USAGE

Indications & Usage: The vitamin B5 essence helps sensitive and dry skin feel moisturized.

DOSAGE & ADMINISTRATION

Dosage & Administration: After using toner, apply an appropriate amount on the entire face and gently pat to promote absorption.